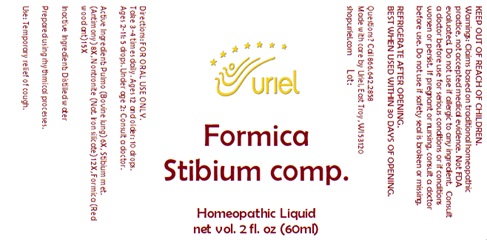 DRUG LABEL: Formica Stibium comp.
NDC: 48951-4200 | Form: LIQUID
Manufacturer: Uriel Pharmacy Inc.
Category: homeopathic | Type: HUMAN OTC DRUG LABEL
Date: 20251117

ACTIVE INGREDIENTS: SUS SCROFA LUNG 6 [hp_X]/1 mL; ANTIMONY 8 [hp_X]/1 mL; SILICON DIOXIDE 12 [hp_X]/1 mL; FORMICA RUFA 15 [hp_X]/1 mL
INACTIVE INGREDIENTS: WATER

Formica Stibium comp.

INDICATIONS AND USAGE

Directions: FOR ORAL USE ONLY.

DOSAGE AND ADMINISTRATION

Take 3-4 times daily. Ages 12 and older: 10 drops. Ages 2-11: 5 drops. Under age 2: Consult a doctor.

Active Ingredient: Pulmo (Bovine lung) 6X, Stibium met. (Antimony) 8X, Nontronite (Nat. Iron silicate) 12X, Formica (Red wood ant) 15X

Inactive Ingredient: Distilled water

Prepared using rhythmical processes.

PURPOSE

Use: Temporary relief of cough.

KEEP OUT OF REACH OF CHILDREN.

WARNINGS

Warnings: Claims based on traditional homeopathic practice, not accepted medical evidence. Not FDA evaluated. Do not use if allergic to any ingredient. Consult a doctor before use for serious conditions or if conditions worsen or persist. If pregnant or nursing, consult a doctor before use. Do not use if safety seal is broken or missing.

REFRIGERATE AFTER OPENING.
BEST WHEN USED WITHIN 30 DAYS OF OPENING.

Questions? Call 866.642.2858
Made with care by Uriel, East Troy, WI 53120
shopuriel.com